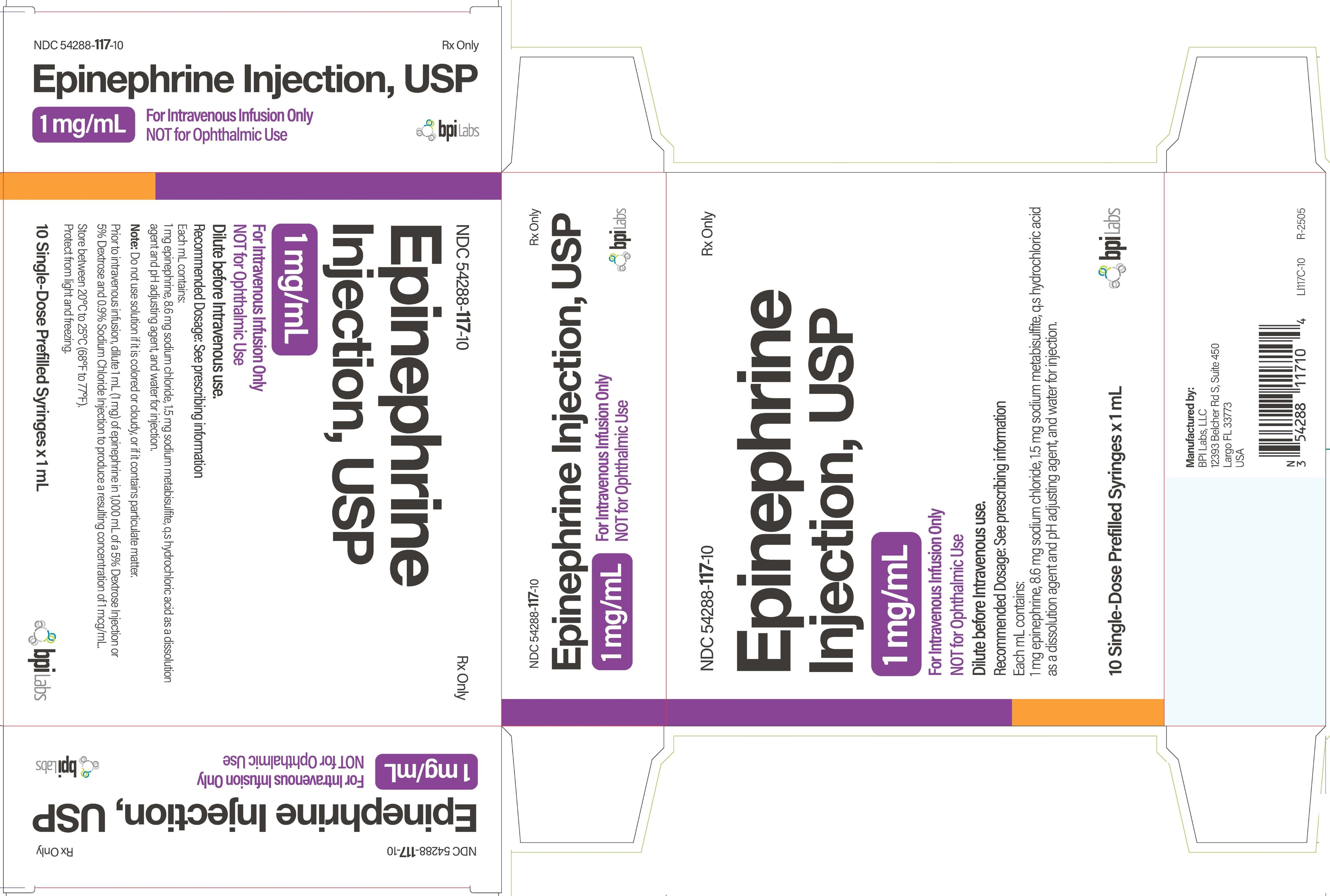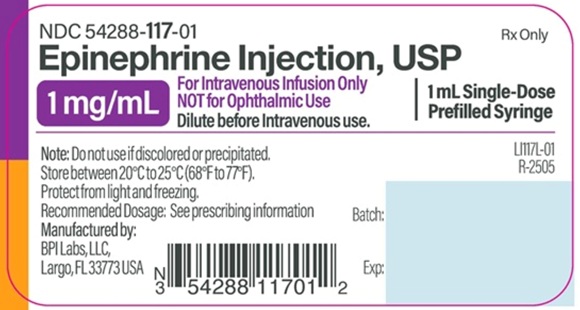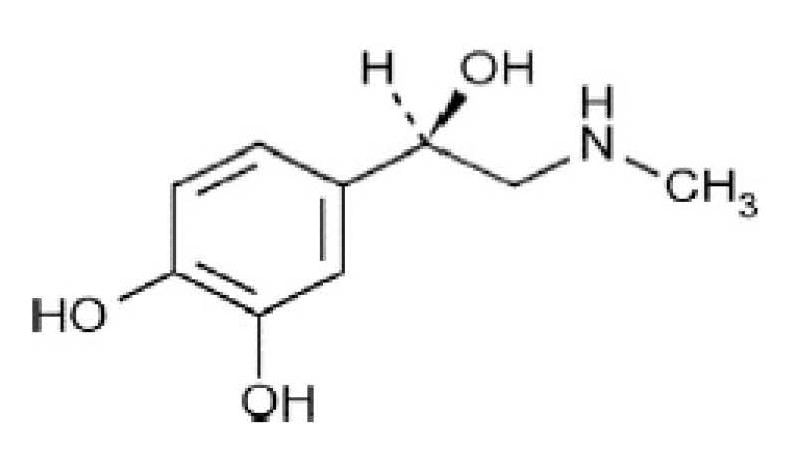 DRUG LABEL: EPINEPHRINE
NDC: 54288-117 | Form: INJECTION
Manufacturer: BPI Labs, LLC
Category: prescription | Type: HUMAN PRESCRIPTION DRUG LABEL
Date: 20251226

ACTIVE INGREDIENTS: EPINEPHRINE 1 mg/1 mL
INACTIVE INGREDIENTS: SODIUM CHLORIDE; SODIUM METABISULFITE; HYDROCHLORIC ACID; WATER

HIGHLIGHTS OF PRESCRIBING INFORMATION

These highlights do not include all the information needed to use EPINEPHRINE INJECTION USP safely and effectively. See full prescribing information for EPINEPHRINE INJECTION USP.
EPINEPHRINE INJECTION, USP for intravenous Infusion only
Initial U.S. Approval: 1939

1 INDICATIONS AND USAGE

Epinephrine is a non-selective alpha and beta adrenergic agonist indicated:

- To increase mean arterial blood pressure in adult patients with hypotension associated with septic shock. (1.1)

2 DOSAGE AND ADMINISTRATION

- Hypotension associated with septic shock (2.2):
  o Dilute epinephrine in dextrose solution prior to infusion.
  o Infuse epinephrine into a large vein.
  o Titrate 0.05 mcg/kg/min to 2 mcg/kg/min to achieve desired blood pressure.
  o Wean gradually.

3 DOSAGE FORMS AND STRENGTHS

Injection solution: 1 mg/mL Syringe.

4 CONTRAINDICATIONS

None

5 WARNINGS AND PRECAUTIONS

- Monitor patient for acute severe hypertension. (5.1)
- Avoid extravasation into tissues, which can cause local necrosis. (5.2)
- Potential for pulmonary edema, which may be fatal. (5.3)
- May constrict renal blood vessels and decrease urine formation. (5.4)
- May induce potentially serious cardiac arrhythmias or aggravate angina pectoris, particularly in patients with underlying heart disease. (5.5)
- Presence of sulfite in this product should not deter use. (5.7)

6 ADVERSE REACTIONS

Most common adverse reactions to systemically administered epinephrine are headache; anxiety; apprehensiveness; restlessness; tremor; weakness; dizziness; sweating; palpitations; pallor; peripheral coldness; nausea/vomiting; and/or respiratory difficulties. Arrhythmias, including fatal ventricular fibrillation, rapid rises in blood pressure producing cerebral hemorrhage, and angina have occurred.

To report SUSPECTED ADVERSE REACTIONS, contact BPI Labs, LLC at (727) 471-0850 or FDA at 1-800-FDA-1088 or www.fda.gov/medwatch.

7 DRUG INTERACTIONS

- Drugs that counter the pressor effects of epinephrine include alpha blockers, vasodilators such as nitrates, diuretics, antihypertensives, and ergot alkaloids. (7)
- Drugs that potentiate the effects of epinephrine include sympathomimetics, beta blockers, tricyclic antidepressants, MAO inhibitors, COMT inhibitors, clonidine, doxapram, oxytocin, levothyroxine sodium, and certain antihistamines. (7)
- Drugs that increase the arrhythmogenic potential of epinephrine include beta blockers, cyclopropane and halogenated hydrocarbon anesthetics, quinidine, antihistamines, exogenous thyroid hormones, diuretics, and cardiac glycosides. Observe for development of cardiac arrhythmias. (7)
- Potassium-depleting drugs, including corticosteroids, diuretics, and theophylline, potentiate the hypokalemic effects of epinephrine. (7)

8 USE IN SPECIFIC POPULATIONS

- Pregnancy: May cause fetal harm (8.1)
- Elderly patients and pregnant women may be at greater risk of developing adverse reactions when epinephrine is administered parenterally. (8.1, 8.5)

FULL PRESCRIBING INFORMATION

1 INDICATIONS AND USAGE

1.1 Hypotension associated with Septic Shock

Epinephrine Injection USP, 1 mg/mL is indicated to increase mean arterial blood pressure in adult patients with hypotension associated with septic shock.

2 DOSAGE AND ADMINISTRATION

2.1 General Considerations

Inspect visually for particulate matter and discoloration prior to administration, whenever solution and container permit. Do not use if the solution is colored or cloudy, or if it contains particulate matter. Discard any unused portion.

2.2 Hypotension associated with Septic Shock

Dilute epinephrine in 5% Dextrose Injection or 5 % Dextrose and 0.9% Sodium Chloride Injection. These dextrose containing fluids provide protection against significant loss of potency by oxidation. Administration in 0.9 % Sodium Chloride Injection alone is not recommended. Whole blood or plasma, if indicated to increase blood volume, should be administered separately.

Add 1 mL (1 mg) of epinephrine from its Syringe to 1,000 mL of a 5% Dextrose containing solution. Each mL of this dilution contains 1 mcg of epinephrine.

Correct blood volume depletion as fully as possible before any vasopressor is administered. When, as an emergency measure, intraaortic pressures must be maintained to prevent cerebral or coronary artery ischemia, epinephrine can be administered before and concurrently with blood volume replacement.

Whenever possible, give infusions of epinephrine into a large vein. Avoid using a catheter tie-in technique, because the obstruction to blood flow around the tubing may cause stasis and increased local concentration of the drug. Occlusive vascular diseases (for example, atherosclerosis, arteriosclerosis, diabetic endarteritis, Buerger’s disease) are more likely to occur in the lower than in the upper extremity; therefore, avoid the veins of the leg in elderly patients or in those suffering from such disorders. There is potential for gangrene in a lower extremity when infusions of catecholamine are given in an ankle vein.

To provide hemodynamic support in septic shock associated hypotension in adult patients, the suggested dosing infusion rate of intravenously administered epinephrine is 0.05 mcg/kg/min to 2 mcg/kg/min, and is titrated to achieve a desired mean arterial pressure (MAP). The dosage may be adjusted periodically, such as every 10 to 15 minutes, in increments of 0.05 mcg/kg/min to 0.2 mcg/kg/min, to achieve the desired blood pressure goal.

Continuous epinephrine infusion is generally required over several hours or days until the patient’s hemodynamic status improves. The duration of perfusion or total cumulative dose cannot be predicted.

After hemodynamic stabilization, wean incrementally over time, such as by decreasing doses of epinephrine every 30 minutes over a 12- to 24-hour period.

3 DOSAGE FORMS AND STRENGTHS

Injection solution: 1 mg/mL epinephrine as a sterile solution in a 1 mL glass syringe, marked Epinephrine Injection USP, 1 mg/mL.

4 CONTRAINDICATIONS

None

5 WARNINGS AND PRECAUTIONS

5.1 Hypertension

When Epinephrine Injection is administered intravenously, titrate the infusion while monitoring vital signs. Invasive arterial blood pressure monitoring and central venous pressure monitoring are recommended. Because of varying response to epinephrine, dangerously high blood pressure may occur [ see Drug Interactions (7)].

5.2 Extravasation and Tissue Necrosis with Intravenous Infusion

When Epinephrine Injection is administered intravenously, the infusion site should be checked frequently for free flow. Avoid extravasation of epinephrine into the tissues, to prevent local necrosis. Blanching along the course of the infused vein, sometimes without obvious extravasation, may be attributed to vasa vasorum constriction with increased permeability of the vein wall, permitting some leakage. This also may progress on rare occasions to superficial slough. Hence, if blanching occurs, consider changing the infusion site at intervals to allow the effects of local vasoconstriction to subside.

Antidote for Extravasation Ischemia:To prevent sloughing and necrosis in areas in which extravasation has taken place, infiltrate the area with 10 mL to 15 mL of saline solution containing from 5 mg to 10 mg of phentolamine, an adrenergic blocking agent. Use a syringe with a fine hypodermic needle, with the solution being infiltrated liberally throughout the area, which is easily identified by its cold, hard, and pallid appearance. Sympathetic blockade with phentolamine causes immediate and conspicuous local hyperemic changes if the area is infiltrated within 12 hours.

5.3 Pulmonary Edema

When Epinephrine Injection is administered intravenously, there is risk of pulmonary edema because of the peripheral constriction and cardiac stimulation produced. Treatment of pulmonary edema consists of a rapidly acting alpha-adrenergic blocking drug (such as phentolamine mesylate) and respiratory support.

5.4 Renal Impairment

Intravenously administered epinephrine initially may produce constriction of renal blood vessels and decrease urine formation.

5.5 Cardiac Arrhythmias and Ischemia

Epinephrine may induce cardiac arrhythmias and angina pectoris in patients, especially patients suffering from coronary artery disease, organic heart disease, cerebrovascular disease, hypertension, or patients who are receiving drugs that sensitize the myocardium [see Adverse Reactions (6) and Drug Interactions (7)]. Treatment of arrhythmias consists of administration of a beta-adrenergic blocking drug (such as propranolol).

5.6 Other Disease Interactions

Epinephrine should be administered with caution to patients with hyperthyroidism, Parkinson’s disease, diabetes mellitus, pheochromocytoma, elderly individuals, and pregnant women. Patients with Parkinson’s disease may experience psychomotor agitation or notice a temporary worsening of symptoms. Diabetic patients may experience transient increases in blood sugar. Despite these concerns, the presence of these conditions is not a contraindication to epinephrine administration in an acute, life-threatening situation.

5.7 Allergic Reactions Associated with Sulfite

Epinephrine is the preferred treatment for serious allergic or other emergency situations even though this product contains sodium metabisulfite, a sulfite that may in other products cause allergic-type reactions including anaphylactic symptoms or life-threatening or less severe asthmatic episodes in certain susceptible persons. The alternatives to using epinephrine in a life-threatening situation may not be satisfactory. The presence of sulfite(s) in this product should not deter administration of the drug for treatment of serious allergic or other emergency situations.

6 ADVERSE REACTIONS

The following adverse reactions associated with the infusion of epinephrine were identified in the literature. Because these reactions are reported voluntarily from a population of uncertain size, it is not always possible to estimate their frequency reliably or to establish a causal relationship to drug exposure.

Cardiovascular disorders: tachycardia, supraventricular tachycardia, ventricular arrhythmias, myocardial ischemia, myocardial infarction, limb ischemia, pulmonary edema

Gastrointestinal disorders: Nausea, vomiting

General disorders and administrative site conditions: Chest pain, extravasation,

Metabolic: hypoglycemia, hyperglycemia, insulin resistance, hypokalemia, lactic acidosis

Nervous system disorders: Headache, nervousness, paresthesia, tremor, stroke, central nervous system bleeding

Psychiatric disorders: Excitability

Renal disorders: Renal insufficiency

Respiratory: Pulmonary edema, rales

Skin and subcutaneous tissue disorders: Diaphoresis, pallor, piloerection, skin blanching, skin necrosis with extravasation

7 DRUG INTERACTIONS

Drugs antagonizing pressor effects of epinephrine

- α-blockers, such as phentolamine
- Vasodilators, such as nitrates
- Diuretics
- Antihypertensives
- Ergot alkaloids

Drugs potentiating pressor effects of epinephrine

- Sympathomimetics
- β-blockers, such as propranolol
- Tricyclic anti-depressants
- Monoamine oxidase (MAO) inhibitors
- Catechol-O-methyl transferase (COMT) inhibitors, such as entacapone
- Clonidine
- Doxapram
- Oxytocin

Drugs potentiating arrhythmogenic effects of epinephrine

Patients who are concomitantly receiving any of the following drugs should be observed carefully for the development of cardiac arrhythmias [see Warnings and Precautions (5.5) and Adverse Reactions (6)].

- β-blockers, such as propranolol
- Cyclopropane or halogenated hydrocarbon anesthetics, such as halothane
- Antihistamines
- Thyroid hormones
- Diuretics
- Cardiac glycosides, such as digitalis glycosides
- Quinidine

Drugs potentiating hypokalemic effects of epinephrine

- Potassium depleting diuretics
- Corticosteroids
- Theophylline

Epinephrine should not be used to counteract circulatory collapse or hypotension caused by phenothiazines, as a reversal of the pressor effects of epinephrine may result in further lowering of blood pressure.

Epinephrine may antagonize the neuronal blockade produced by guanethidine resulting in decreased antihypertensive effect and requiring increased dosage of the latter.

8 USE IN SPECIFIC POPULATIONS

8.1 Pregnancy

Risk Summary

Prolonged experience with epinephrine use in pregnant women over several decades, based on published literature, does not identify a drug-associated risk of major birth defects, miscarriage, or adverse maternal or fetal outcomes. However, there are risks to the mother and fetus associated with epinephrine use during labor or delivery (see Clinical Considerations). In animal reproduction studies, epinephrine administered by the subcutaneous route to pregnant rabbits, mice, and hamsters, during the period of organogenesis, resulted in adverse developmental effects (including gastroschisis, embryonic lethality, and delayed skeletal ossification) at doses approximately 2 times the maximum recommended daily intramuscular, subcutaneous, or intravenous dose (see Data).

The estimated background risk of major birth defects and miscarriage for the indicated population is unknown. All pregnancies have a background risk of birth defect, loss, or other adverse outcomes. In the United States general population, the estimated background risk of major birth defects and miscarriage in clinically recognized pregnancies is 2 to 4% and 15 to 20%, respectively.

Clinical Considerations

Disease-associated maternal and/or embryo/fetal risk

Hypotension associated with septic shock is a medical emergency in pregnancy which can be fatal if left untreated. Delaying treatment in pregnant women with hypotension associated with septic shock may increase the risk of maternal and fetal morbidity and mortality. Life-sustaining therapy for the pregnant woman should not be withheld due to potential concerns regarding the effects of epinephrine on the fetus.

Labor or Delivery

Epinephrine usually inhibits spontaneous or oxytocin-induced contractions of the pregnant human uterus and may delay the second stage of labor. Avoid epinephrine during the second stage of labor. In dosage sufficient to reduce uterine contractions, the drug may cause a prolonged period of uterine atony with hemorrhage. Avoid epinephrine in obstetrics when maternal blood pressure exceeds 130/80 mmHg.

Although epinephrine may improve maternal hypotension associated with septic shock and anaphylaxis, it may result in uterine vasoconstriction, decreased uterine blood flow, and fetal anoxia.

Data

Animal Data

In an embryofetal development study with pregnant rabbits dosed during the period of organogenesis (on days 3 to 5, 6 to 7, or 7 to 9 of gestation), epinephrine caused teratogenic effects (including gastroschisis) at doses approximately 15 times the maximum recommended intramuscular, subcutaneous, or intravenous dose (on a mg/m ^2 basis at a maternal subcutaneous dose of 1.2 mg/kg/day for 2 to 3 days). Animals treated on days 6 to 7 had decreased number of implantations.

In an embryofetal development study, pregnant mice were administered epinephrine (0.1 to 10 mg/kg/day) on Gestation Days 6 to 15. Teratogenic effects, embryonic lethality, and delays in skeletal ossification were observed at approximately 3 times the maximum recommended intramuscular, subcutaneous, or intravenous dose (on a mg/m ^2 basis at maternal subcutaneous dose of 1 mg/kg/day for 10 days). These effects were not seen in mice at approximately 2 times the maximum recommended daily intramuscular or subcutaneous dose (on a mg/m ^2 basis at a subcutaneous maternal dose of 0.5 mg/kg/day for 10 days).

In an embryofetal development study with pregnant hamsters dosed during the period of organogenesis from gestation days 7 to 10, epinephrine produced reductions in litter size and delayed skeletal ossification at doses approximately 2 times the maximum recommended intramuscular, subcutaneous, or intravenous dose (on a mg/m ^2 basis at a maternal subcutaneous dose of 0.5 mg/kg/day).

8.2 Lactation

Risk Summary

There is no information regarding the presence of epinephrine in human milk or the effects of epinephrine on the breastfed infant or on milk production. However, due to its poor oral bioavailability and short half-life, epinephrine exposure is expected to be very low in the breastfed infant.

8.4 Pediatric Use

Safety and effectiveness of epinephrine in pediatric patients with septic shock have not been established.

8.5 Geriatric Use

Clinical studies of epinephrine for the treatment of hypotension associated with septic shock did not include sufficient numbers of subjects aged 65 and over to determine whether they respond differently from younger subjects. Other reported clinical experience has not identified differences in responses between the elderly and younger patients. In general, dose selection for an elderly patient should be cautious, usually starting at the low end of the dosing range, reflecting the greater frequency of decreased hepatic, renal, or cardiac function, and of concomitant disease or other drug therapy.

10 OVERDOSAGE

Overdosage of epinephrine may produce extremely elevated arterial pressure, which may result in cerebrovascular hemorrhage, particularly in elderly patients. Overdosage may also result in pulmonary edema because of peripheral vascular constriction together with cardiac stimulation. Epinephrine overdosage may also cause transient bradycardia followed by tachycardia and these may be accompanied by potentially fatal cardiac arrhythmias. Premature ventricular contractions may appear within one minute after injection and may be followed by multifocal ventricular tachycardia (prefibrillation rhythm). Subsidence of the ventricular effects may be followed by atrial tachycardia and occasionally by atrioventricular block. Myocardial ischemia and infarction, cardiomyopathy, extreme pallor and coldness of the skin, metabolic acidosis due to elevated blood lactic acid levels, and renal insufficiency and failure have also been reported.

Epinephrine is rapidly inactivated in the body and treatment following overdose is primarily supportive. Treatment of pulmonary edema consists of a rapidly acting alpha-adrenergic blocking drug (such as phentolamine mesylate) and respiratory support. Treatment of arrhythmias consists of administration of a beta-adrenergic blocking drug (such as propranolol). If necessary, pressor effects may be counteracted by rapidly acting vasodilators (such as nitrites) or alpha-adrenergic blocking drugs. If prolonged hypotension follows such measures, it may be necessary to administer another pressor drug.

11 DESCRIPTION

Epinephrine Injection USP is a clear, colorless, sterile solution containing 1 mg/mL epinephrine, packaged as a 1 mL solution in a 1 mL single dose syringe. Each mL of Epinephrine Injection, USP solution contains 1 mg epinephrine, 8.6 mg sodium chloride, 1.5 mg sodium metabisulfite, q.s hydrochloric acid as a dissolution and pH adjustment, and water for injection. The pH range is 2.2-5.0.

Solution must be diluted prior to intravenous use.

Epinephrine is a sympathomimetic catecholamine. The chemical name of epinephrine is: 1,2- Benzenediol, 4-[(1R)-1-hydroxy-2-(methylamino)ethyl]-, or (-)-3,4-Dihydroxy- α-[2- (methylamino)ethyl]benzyl alcohol. The chemical structure of epinephrine is:

The molecular weight of epinephrine is 183.2.

Epinephrine solution deteriorates rapidly on exposure to air or light, turning pink from oxidation to adrenochrome and brown from the formation of melanin.

12 CLINICAL PHARMACOLOGY

12.1 Mechanism of Action

Epinephrine acts on both alpha (α)- and beta (β)-adrenergic receptors. The mechanism of the rise in blood pressure is 3-fold: a direct myocardial stimulation that increases the strength of ventricular contraction (positive inotropic action), an increased heart rate (positive chronotropic action), and peripheral vasoconstriction.

12.2 Pharmacodynamics

Intravenous use for hypotension associated with septic shock

Following intravenous administration of epinephrine, increases in systolic blood pressure and heart rate are observed. Decreases in systemic vascular resistance and diastolic blood pressure are observed at low doses of epinephrine because of β 2-mediated vasodilation, but are overtaken by α 1-mediated peripheral vasoconstriction at higher doses leading to increase in diastolic blood pressure. The onset of blood pressure increase following an intravenous dose of epinephrine is < 5 minutes and the time to offset blood pressure response occurs within 20 min. Most vascular beds are constricted including renal, splanchnic, mucosal and skin.

12.3 Pharmacokinetics

When administered parenterally, epinephrine has a rapid onset and short duration of action.

Following intravenous injection, epinephrine is rapidly cleared from the plasma with an effective half-life of < 5 min. A pharmacokinetic steady state following continuous intravenous infusion is achieved within 10-15 min. In patients with septic shock, epinephrine displays dose-proportional pharmacokinetics in the infusion dose range of 0.03 to 1.7 mcg/kg/min.

Epinephrine is extensively metabolized with only a small amount excreted unchanged.

Epinephrine is rapidly degraded to vanillylmandelic acid, an inactive metabolite, by monoamine oxidase and catechol-O-methyltransferase that are abundantly expressed in the liver, kidneys and other extraneuronal tissues. The tissues with the highest contribution to removal of circulating exogenous epinephrine are the liver (32%), kidneys (25%), skeletal muscle (20%), and mesenteric organs (12%).

Special Populations

Elderly

In a pharmacokinetic study of 45-minute epinephrine infusions given to healthy men aged 20 to 25 years and healthy men aged 60 to 65 years, the mean plasma metabolic clearance rate of epinephrine at steady state was greater among the older men (144.8 versus 78 mL/kg/min for a 14.3 ng/kg/min infusion).

Body Weight

Body weight has been found to influence epinephrine pharmacokinetics. Higher body weight was associated with a higher plasma epinephrine clearance and a lower concentration plateau.

13 NONCLINICAL TOXICOLOGY

13.1 Carcinogenesis, Mutagenesis, Impairment of Fertility

Long-term studies to evaluate the carcinogenic potential of epinephrine have not been conducted.

Epinephrine and other catecholamines have been shown to have mutagenic potential in vitro. Epinephrine was positive in the Salmonella bacterial reverse mutation assay, positive in the mouse lymphoma assay, and negative in the in vivomicronucleus assay. Epinephrine is an oxidative mutagen based on the E. coliWP2 Mutoxitest bacterial reverse mutation assay. This should not prevent the use of epinephrine under the conditions noted under the Indications and Usage.

The potential for epinephrine to impair reproductive performance has not been evaluated, but epinephrine has been shown to decrease implantation in female rabbits dosed subcutaneously with 1.2 mg/kg/day (15-fold the highest human intramuscular or subcutaneous daily dose) during gestation days 3 to 9.

13.2 Animal Toxicology and/or Pharmacology

Epinephrine was associated with metabolic effects, decreased mesentery, coronary and renal conductance in a sheep model of septic shock. Data from hemolysis study have shown that epinephrine at 1:1000 dilution is non-hemolytic. Epinephrine infusion significantly increased the MAP (69 vs. 86 mmHg) and cardiac output (6.4 vs. 7.1 L/min) and decreased renal blood flow (330 vs. 247 mL/min).

14 CLINICAL STUDIES

14.1 Hypotension associated with Septic Shock

Fourteen clinical studies from the literature documented that epinephrine increases the mean arterial pressure (MAP) in patients with hypotension associated with septic shock.

16 HOW SUPPLIED/STORAGE AND HANDLING

Epinephrine 1 mg/mL Injection is a clear, colorless solution available as follows :

NDC 54288-117-10 10 Single-Dose Prefilled Syringes Containing 1 mL

Epinephrine is light sensitive. Protect from light until ready to use.

Do not refrigerate. Protect from freezing.

Store at room temperature, between 20°C to 25°C (68°F to 77°F). (See USP Controlled Room Temperature.) Protect from alkalis and oxidizing agents.

Revised: December 2024

Manufactured by:
BPI Labs LLC
12393 Belcher Rd S, Suite 450,
Largo, FL 33773

LI11I
R-2412

PACKAGE LABEL PRINCIPAL DISPLAY PANEL

Label
Epinephrine Injection, USP 1 mg/mL
NDC 54288-117-01

Carton
Epinephrine Injection, USP 1 mg/mL
NDC 54288-117-10